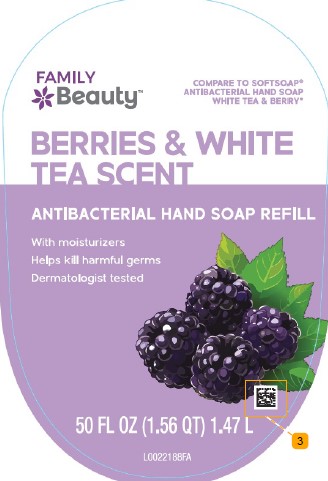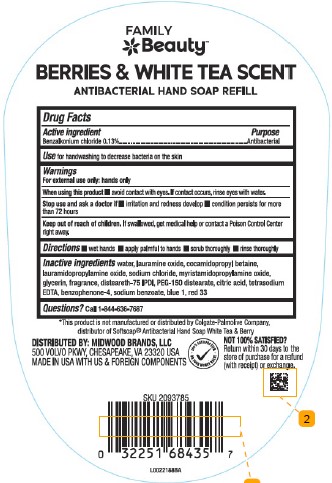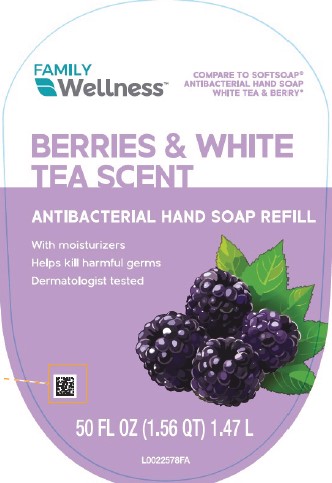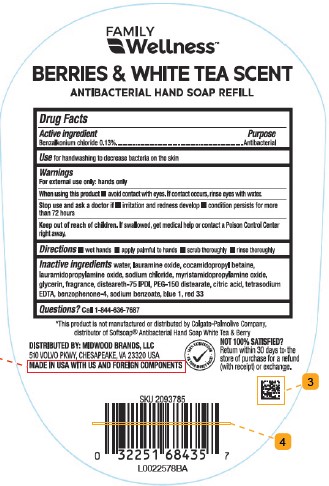 DRUG LABEL: Benzalkonium Chloride
NDC: 55319-879 | Form: GEL
Manufacturer: Family Dollar Stores, Inc
Category: otc | Type: HUMAN OTC DRUG LABEL
Date: 20260211

ACTIVE INGREDIENTS: BENZALKONIUM CHLORIDE 1.3 mg/1 mL
INACTIVE INGREDIENTS: WATER; LAURAMINE OXIDE; COCAMIDOPROPYL BETAINE; LAURAMIDOPROPYLAMINE OXIDE; SODIUM CHLORIDE; MYRISTAMIDOPROPYLAMINE OXIDE; GLYCERIN; DISTEARETH-75 ISOPHORONE DIISOCYANATE; PEG-150 DISTEARATE; CITRIC ACID MONOHYDRATE; EDETATE SODIUM; SULISOBENZONE; SODIUM BENZOATE; FD&C BLUE NO. 1; D&C RED NO. 33

Family Beauty_Family Wellness 897.003/897AC
Antibacterial Hand Soap Berries & White Tea

Claims

FAMILY Wellness™

BERRIES & WHITE TEA SCENT

ANTIBACTERIAL HAND SOAP REFILL

Active ingredient

Benzalkonium Chloride 0.13%

Purpose

Antibacterial

Use

for handwashing to decrease bacteria on the skin

Warnings

For external use only: hands only

When using this product

- avoid conctact with eyes. If contact occurs, rinse eyes with water.

Stop use and ask a doctor if

- irritation and redness develop
- condition persists for more than 72 hours

Keep out of reach of children.

If swallowed, get medical help or contact a Poison Control Center right away.

Directions

- wet hands
- apply palmful to hands
- scrub thoroughly
- rinse thoroughly

Inactive ingredients

water, lauramine oxide, cocamidopropyl betaine, lauramidopropylamine oxide, sodium chloride, myristamidopropylamine oxide, glycerin, fragrance, disteareth-75 IPDI, PEG-150 distearate, citric acid, tetrasodium EDTA, benzophenone-4, sodium benzoate, blue 1, red 33

Questions?

Call 1-844-636-7687

Disclaimer

*This product is not manufactured or distributed by the Colgate-Palmolive Company, distributor of Softsoap® Antibacterial Hand Soap White Tea & Berry.

ADVERSE REACTION

DISTRIBUTED BY: MIDWOOD BRANDS, LLC

500 VOLVO PKWY, CHESAPEAKE, VA 23320 USA

MADE IN USA WITH US & FOREIGN COMPONENTS

100% SATISFACTION OR YOUR MONEY BACK!

NOT 100% SATISFIED?

Return within 30 days to the store of purchase for a refund (with receipt) or exchange.

principal display panel

FAMILY Wellness™

COMPARE TO SOFTSOAP®ANTIBACTERIAL HAND SOAP WHITE TEA & BERRY*

BERRIES & WHITE TEA SCENT

ANTIBACTERIAL HAND SOAP REFILL

With moisturizers

Helps kill harmful germs

Dermatologist tested

50 FL OZ (1.56 QT) 1.47 L

principal display panel

FAMILY Beauty™

COMPARE TO SOFTSOAP®ANTIBACTERIAL HAND SOAP WHITE TEA & BERRY*

BERRIES & WHITE TEA SCENT

ANTIBACTERIAL HAND SOAP REFILL

With moisturizers

Helps kill harmful germs

Dermatologist tested

50 FL OZ (1.56 QT) 1.47 L